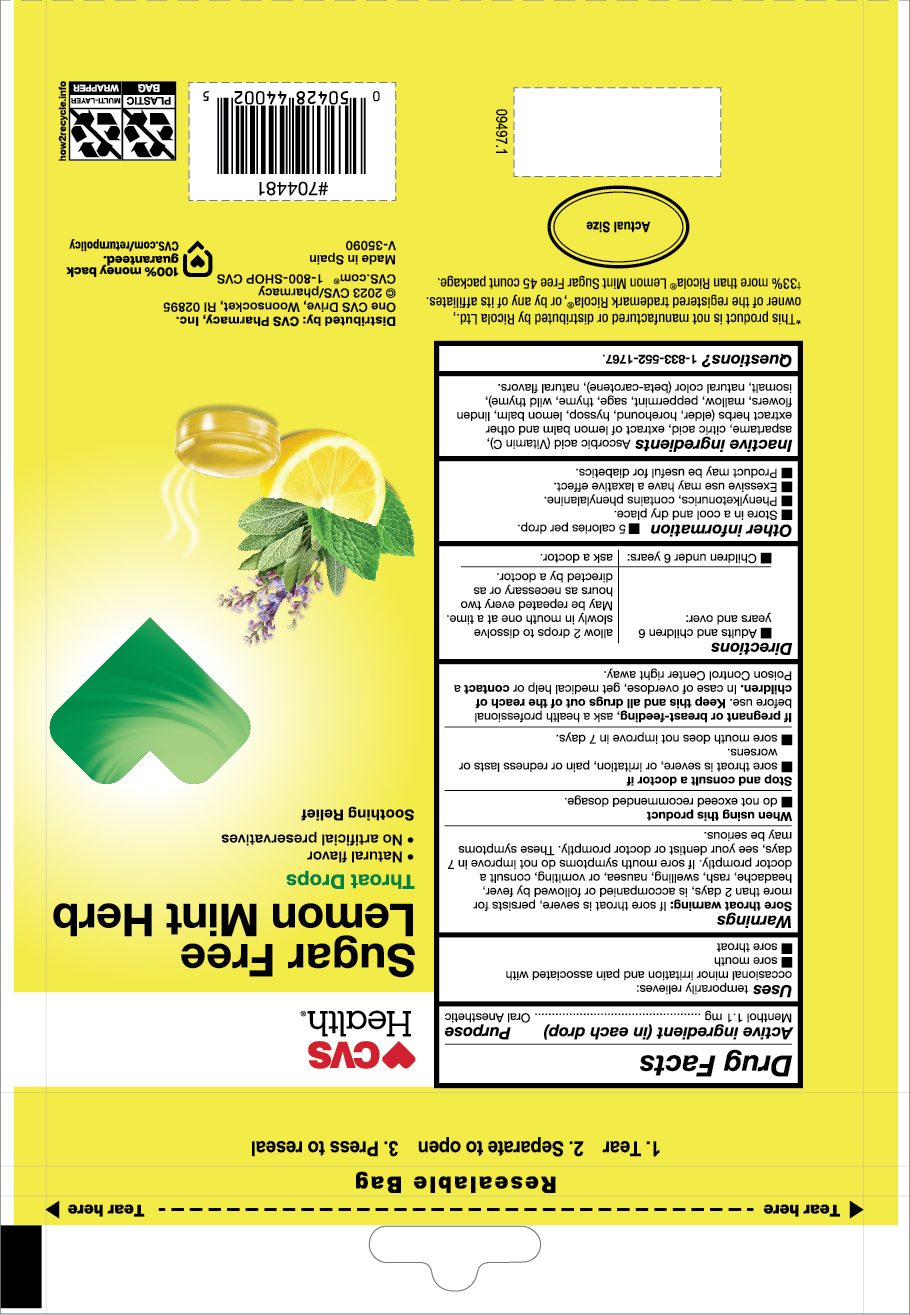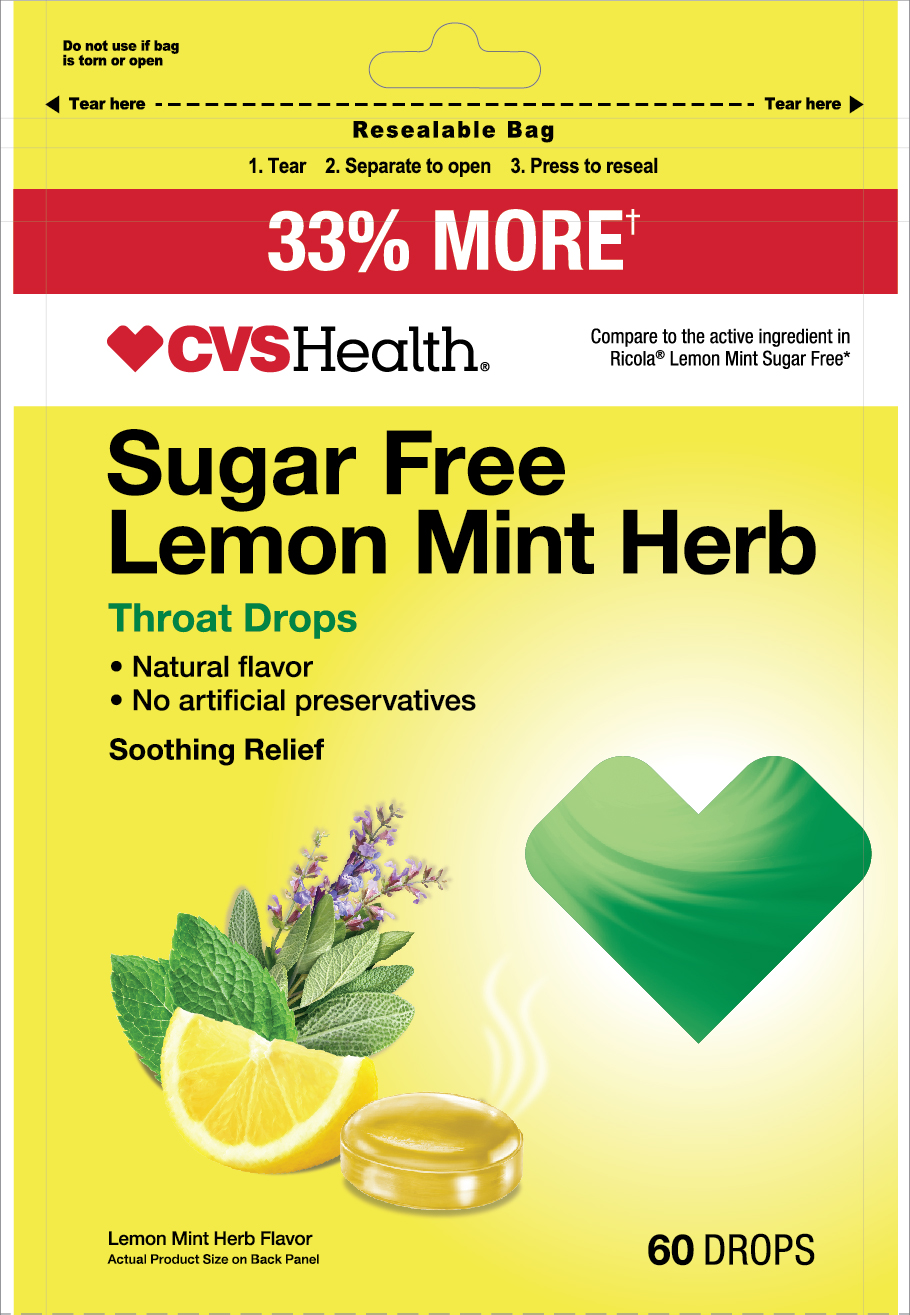 DRUG LABEL: Lemon Mint Herb Throat Drops
NDC: 51316-852 | Form: PASTILLE
Manufacturer: CVS Pharmacy
Category: otc | Type: HUMAN OTC DRUG LABEL
Date: 20241007

ACTIVE INGREDIENTS: MENTHOL 1.1 mg/1 1
INACTIVE INGREDIENTS: PEPPERMINT; HOREHOUND; MELISSA OFFICINALIS FLOWER; THYME; TILIA CORDATA FLOWER; SAGE; MALVA SYLVESTRIS LEAF; CITRIC ACID MONOHYDRATE; ASCORBIC ACID; ASPARTAME; SAMBUCUS NIGRA FLOWER; HYSSOPUS OFFICINALIS FLOWERING TOP; WILD THYME; ISOMALT; BETA CAROTENE

Natural Herb Cough Drops

Active Ingredient:

- Menthol 1.1 mg.............oral anesthetic

PURPOSE

Uses temporarily relieves:

ocassional minor irritation and pain associated with:

- sore mouth
- sore throat

INDICATIONS AND USAGE

Uses temporarily relieves:

ocassional minor irritation and pain associated with:

- sore mouth
- sore throat

Warnings

Sore throat warning: severe or persistence sore throat accompanied by high fever, headache, nausea and vomiting may be serious. Consult a doctor promptly. If sore mouth symptons does not improve in 7 days see your dentist or doctor promptly. These symptoms maybe serious.

Stop and consult a doctor if

- sore throat is severe, or irritation, pain or redness last or worseness
- sore mouh does not improve in 7 days

Stop use and consult a doctor if

- sore mouth symptons do not improve in 7 days or if irritation, pains or redness persists or worsens.

PREGNANCY OR BREAST FEEDING

If pregnant or breast-feeding, ask a health professional before use.

KEEP OUT OF REACH OF CHILDREN

Keep this and all drugs out of the reach of children.

OVERDOSAGE

In case of accidental overdose, get medical help or contact a Poison Control Center right away.

Directions

- Adults and children 6 years and over: dissolve 2 drop slowly in mouth one at a time. Maybe repeated every 2 hours as needed or as directed by a doctor.
- Children under 6 years as a Doctor

OTHER SAFETY INFORMATION

- Store in a cool and dry place
- 5 calories per drop
- Phenylketonurics, contains phenylalanine
- Excessive use may have a laxative effect
- Product maybe useful for diabetics

INACTIVE INGREDIENT

ascorbic acid (Vitamin C), aspartame, citric acid, extract of lemon balm, and other extracts herbs (elderflower, horehound, hyssop, lemon balm, linden flowers, mallow, peppermint, sage, thyme. wild thyme) isomalt, natural color (beta carotene), natural flavors

QUESTIONS

Questions? or to report and adverse event call: 1-833-552-1767